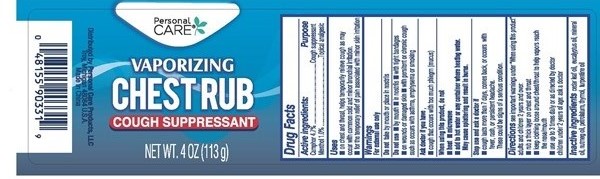 DRUG LABEL: Vaporizing Chest
                        
NDC: 29500-9233 | Form: SALVE
Manufacturer: Personal Care Products
Category: otc | Type: HUMAN OTC DRUG LABEL
Date: 20170224

ACTIVE INGREDIENTS: CAMPHOR (SYNTHETIC) 5.31 g/113 g; MENTHOL 1.13 g/113 g
INACTIVE INGREDIENTS: EUCALYPTUS OIL; CEDAR LEAF OIL; MINERAL OIL; NUTMEG OIL; PETROLATUM; THYMOL; TURPENTINE

Vaporizing Chest - 9233

Drug Facts Active Ingredients

Camphor 4.7%

Menthol 1.0%

Purpose

Cough suppressant

Topical analgesic

Keep out of reach of children

children under 2 years of age: ask a doctor

Directions

see important warnings under "When using this product"
adults and children 2 years and over.

- rub a thick layer on chest and throat

- keep clothing loose around chest/throat to help vapors reach the nose/mouth

- use up to 3 times daily or as directed by doctor

Inactive Ingredients

eucalyptus oil, cedar leaf oil, mineral oil, nutmeg oil, petrolatum, thymol, turpentine oil

Warnings

For external use only

Do not take by mouth or place in nostrils

Do not use

- by mouth
- in nostrils
- with tight bandages
- on wounds or damaged skin
- with persistant or chronic cough such as occurs with asthma, emphysema or smoking

Ask a doctor if you have

- cough that occurs with too much phlegm (mucus)

When using this product, do not

- heat
- microwave
- add to hot water or any container where heating water

May cause splattering and result in burns.

Stop use and ask a doctor if

- cough lasts more than 7 days, comes back, or occurs with fever, rash, or persistant headache.

These could be signs of a serious condition

Uses

- on chest and throat, helps temporarily relieve cough as may occur with common cold and minor bronchial irritation.
- for the temporary relief of pain associated with minor skin irritations

PACKAGE LABEL

Personal Care

Vaporizing Chest Rub

Cough Suppressant

Net Wt. 4 oz (113 g)

Distributed by Personal Care Products, LLC
Troy, Michigan 48084 U.S.A.
Made in China